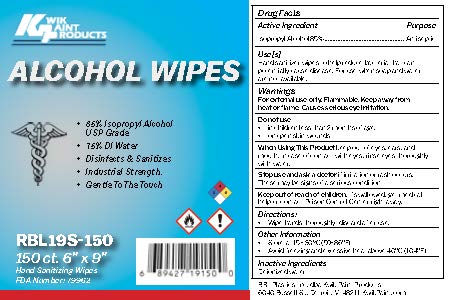 DRUG LABEL: Hand Sanitizer
NDC: 79962-001 | Form: CLOTH
Manufacturer: RBL Plastics
Category: otc | Type: HUMAN OTC DRUG LABEL
Date: 20220113

ACTIVE INGREDIENTS: ISOPROPYL ALCOHOL 0.85 1/1 1
INACTIVE INGREDIENTS: WATER

RBL Plastics

Active Ingredient(s)

Isopropyl Alcohol 85% Purpose: Antiseptic

Purpose

Antiseptic, Hand Sanitizer

Use

Hand Sanitizer to help reduce bacteria that potentially can cause disease. For use when soap and water are not available.

Warnings

For external use only. Flammable. Keep away from heat or flame. Causes serious eye irritation

Do not use

- in children less than 2 months of age
- on open skin wounds

When using this product keep out of eyes, ears, and mouth. In case of contact with eyes, rinse eyes thoroughly with water.
Stop use and ask a doctor if irritation or rash occurs. These may be signs of a serious condition.
Keep out of reach of children. If swallowed, get medical help or contact a Poison Control Center right away.

Stop use and ask a doctor if irritation or rash occurs. These may be signs of a serious condition.

Keep out of reach of children. If swallowed, get medical help or contact a Poison Control Center right away.

Directions

- Wipe hands thoroughly; discard after use.

Other information

- Store between 15-30C (59-86F)
- Avoid freezing and excessive heat above 40C (104F)

Inactive ingredients

Dionized water

Package Label - Principal Display Panel

150 Count NDC: 79962-001-01